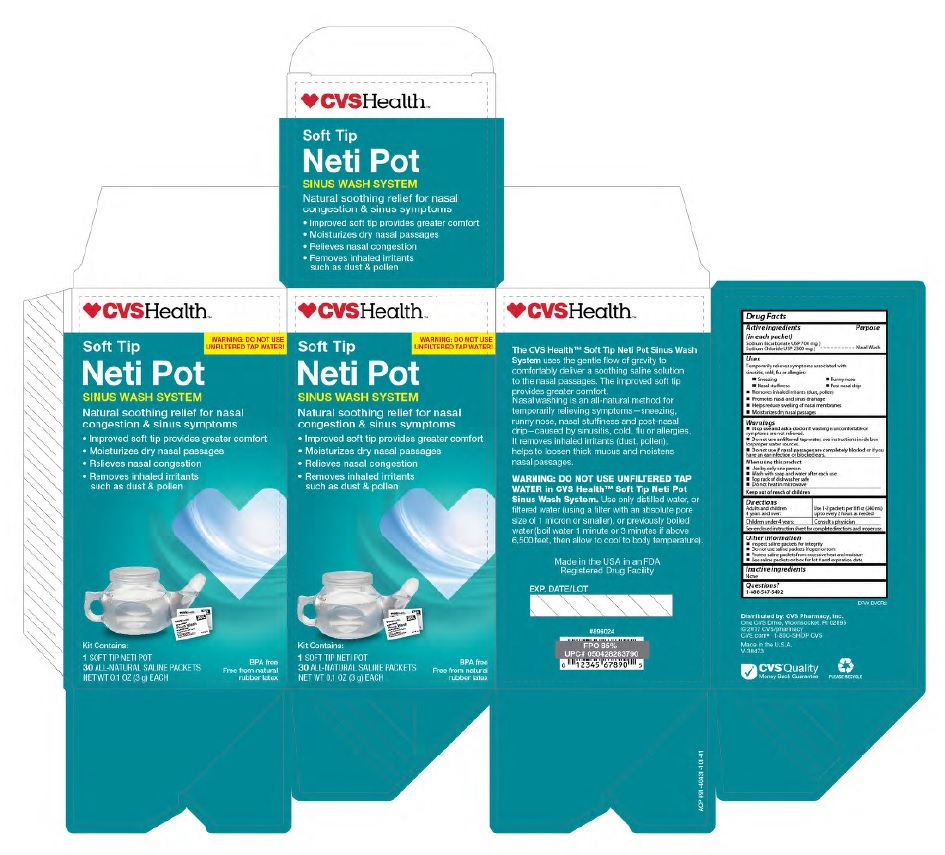 DRUG LABEL: CVS
NDC: 69842-349 | Form: KIT | Route: NASAL
Manufacturer: CVS Pharmacy
Category: otc | Type: HUMAN OTC DRUG LABEL
Date: 20250203

ACTIVE INGREDIENTS: SODIUM BICARBONATE 22.8 mg/100 mg; SODIUM CHLORIDE 77.8 mg/100 mg
INACTIVE INGREDIENTS: WATER

Sinus Wash- Soft Tip Netipot

Purpose

Nasal wash

Uses

Temporarily relieves symptoms associated with sinusitis, cold, flu or allergies

-Sneezing

-Nasal Stuffiness

-Runny Nose

-Post nasal drip

-Removes inhaled irritants (dust, pollen)

-Promotes nasal and sinus drainage

-Helps reduce swelling of nasal membranes

-Moisturizes dry nasal passages

Keep out of reach of children

Warnings

Stop use and ask a doctor if washing is uncomfortable or symptoms are not releived

Directions

Adults and children 4 years and over: use 1-2 packets per 8 oz container every 2 hours as needed

Children under 4 years: consult a physician

Consult Instructions for Use inside box for proper use

When using this product:

-Use by only one person

-Wash with soap and water after each use

-Top rack of dishwasher safe

-Do not heat in microwave

Instructions for Use:
Directions: Read through entire section before using for the first time.
1. Empty the contents of one Saline Sinus Wash packet into the Saline Sinus Wash Neti Pot. First-time users should start with 1/2 packet of the dry ingredients. As you become
more accustomed to the system, work up to using 1 full packet. Additional packets may be purchased from your nearest pharmacy.
2. Fill the pot halfway or to the middle of the indentation with proper water. This makes 1/2 cup (4 oz) solution.
3. Stir thoroughly until dry ingredients have completely dissolved.
4. Proper head position allows solution to run through the nose by gravity.
-Lean over the sink so that the right nostril is directly above the left. The forehead should remain higher than the chin. Raise the handle of the pot so that the solution enters the right nostril. In a few
moments, the solution will begin to drain out of the left nostril into the sink. Do not inhale or "snort" solution into the nose - breathe through your mouth.
5. When the pot is empty, exhale through both nostrils to clear them of excess mucous and solution. Gently blow your nose into a tissue.
6. Repeat the procedure on the other side.
7. Thoroughly rinse the pot after each use with water that has been distilled, sterilized, filtered or previously boiled and leave the pot to air dry thoroughly. The Sinus Wash Neti pot is top-rack
dishwasher safe.

Active Ingredients

(in each packet)

Sodium Bicarbonate USP 700 mg

Sodium Chloride USP 2300 mg

Inactive Ingredients

None